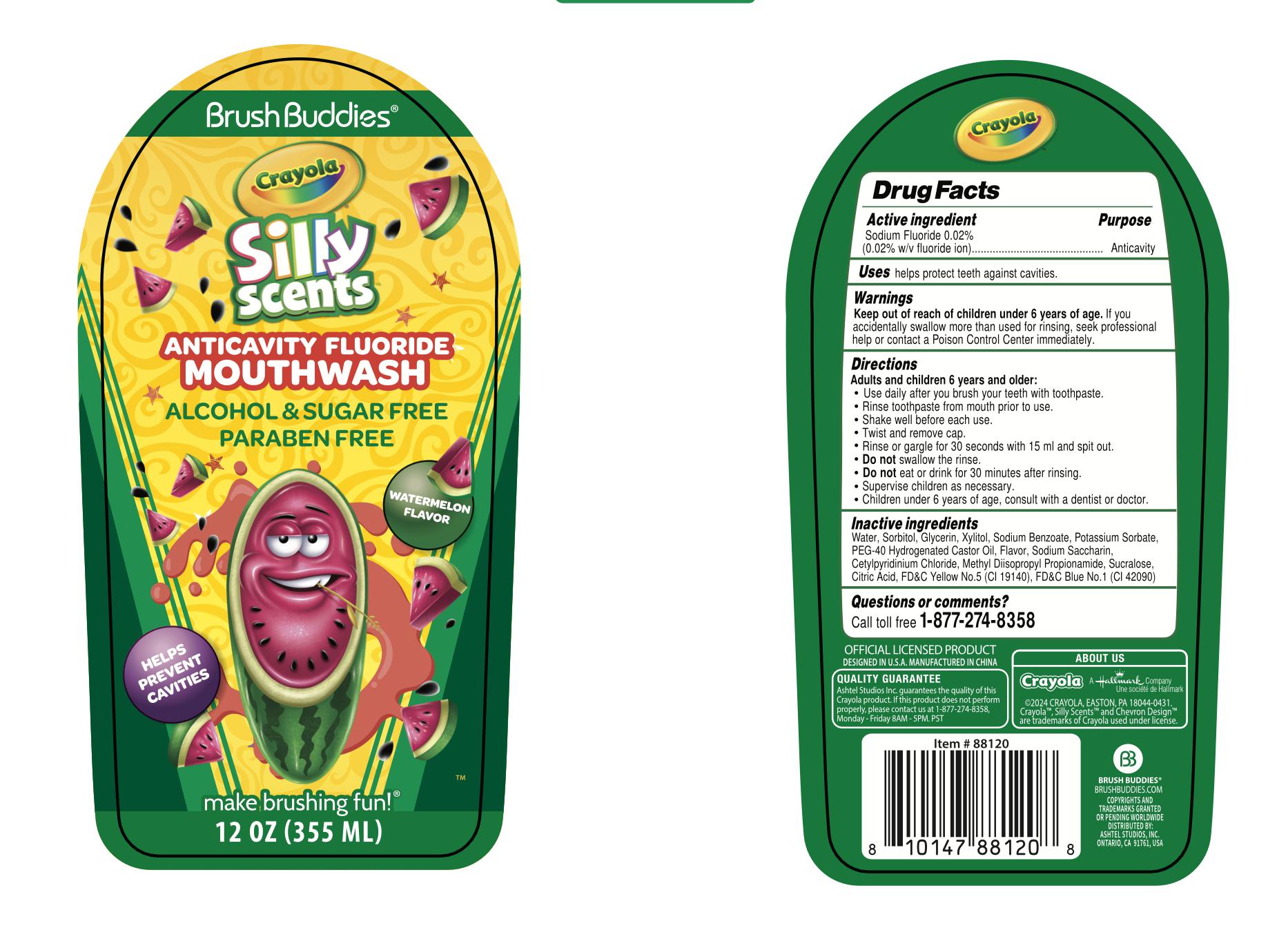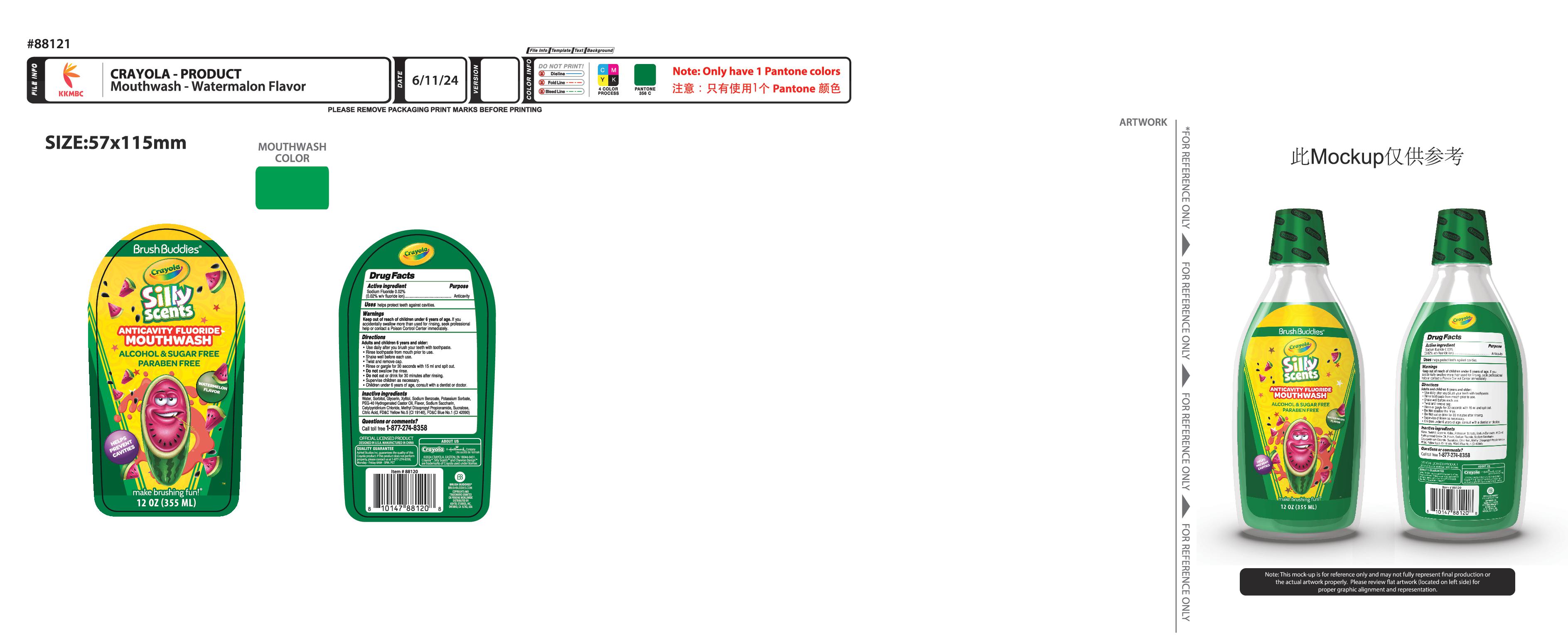 DRUG LABEL: BRUSH BUDDIES CRAYOLA ANTICAVITY FLUORIDE WATERMELON
NDC: 73928-041 | Form: LIQUID
Manufacturer: Kingkey MBC Life Technology Group co., LTD
Category: otc | Type: HUMAN OTC DRUG LABEL
Date: 20251211

ACTIVE INGREDIENTS: SODIUM FLUORIDE 0.02 g/100 mL
INACTIVE INGREDIENTS: POLYOXYL 40 HYDROGENATED CASTOR OIL; SUCRALOSE; METHYL DIISOPROPYL PROPIONAMIDE; POTASSIUM SORBATE; GLYCERIN; XYLITOL; SACCHARIN SODIUM; WATER; CETYLPYRIDINIUM CHLORIDE; FD&C YELLOW NO. 5; FD&C BLUE NO. 1; SORBITOL; SODIUM BENZOATE; CITRIC ACID MONOHYDRATE

BRUSH BUDDIES CRAYOLA ANTICAVITY FLUORIDE WATERMELON（0.02%)

Active ingredient

SODIUM FLUORIDE 0.02%

Purpose

(0.02% w/v fluoride ion)---------Anticavity

Uses

helps protect teeth against cavities

Warnings

Keep out of reach of children under 6 years of age.If you accidentally swallow more than used for rinsing, seek professional help or contact a Poison Control Center immediately.

Directions

Adults and children 6 years and older:
Use daily after you brush your teeth with toothpaste.
Rinse toothpaste from mouth prior to use.
Shake well before each use.
Twist and remove cap.
Rinse or gargle for 30 seconds with 15 ml and spit out
Do Notswallow the rinse.
Do Noteat or drink for 30 minutes after rinsing.
Supervise children as necessary.
Children under 6 years of age, consult with a dentist or doctor.

Inactive ingrdients

WATER
SORBITOL
GLYCERIN
XYLITOL
POTASSIUM SORBATE
SODIUM BENZOATE
PEG-40 HYDROGENATED CASTOR OIL
FLAVOR
SODIUM SACCHARIN
CETYLPYRIDINIUM CHLORIDE

METHYL DIISOPROPYL PROPIONAMIDE
SUCRALOSE
CITRIC ACID
FD&C Yellow No.5（CI 19140）
FD&C Blue No.1（CI 42090）

Questions or comments?

Call toll free 1-877-274-8358